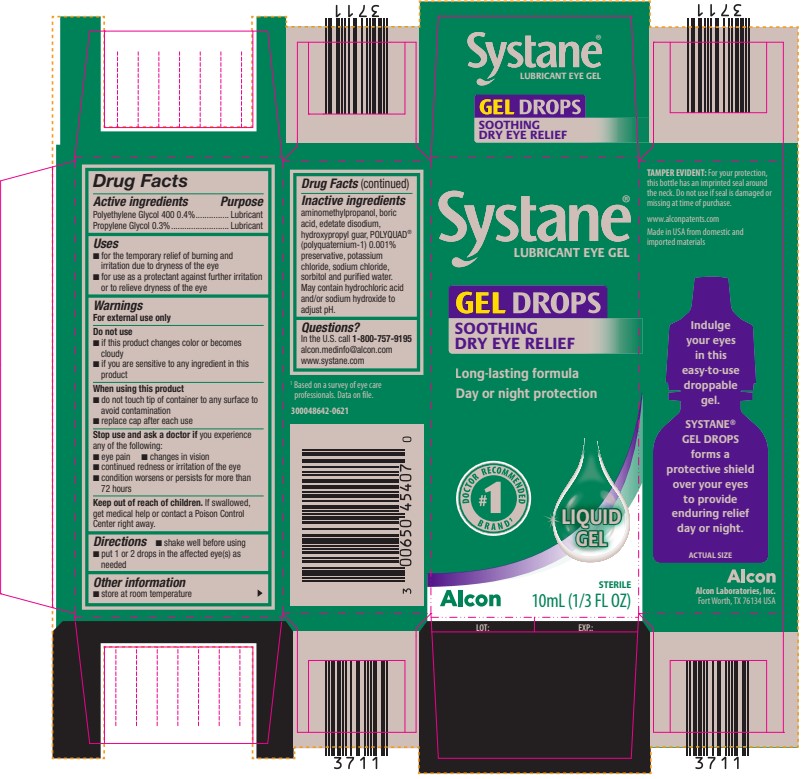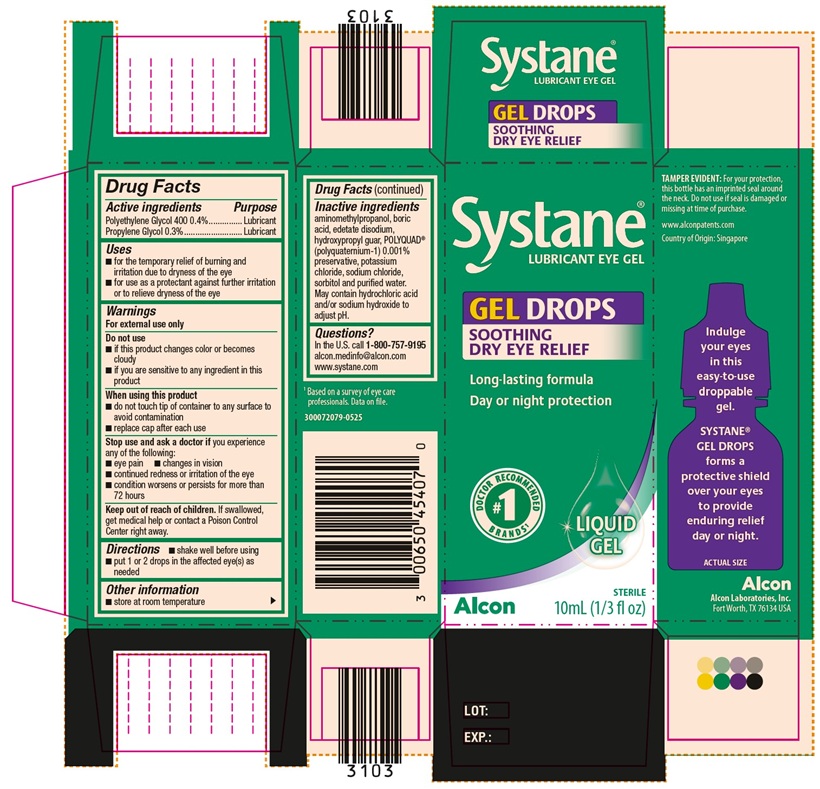 DRUG LABEL: Systane
NDC: 0065-0454 | Form: GEL
Manufacturer: Alcon Laboratories, Inc.
Category: otc | Type: HUMAN OTC DRUG LABEL
Date: 20250730

ACTIVE INGREDIENTS: Polyethylene Glycol 400 4 mg/1 mL; Propylene Glycol 3 mg/1 mL
INACTIVE INGREDIENTS: Aminomethylpropanol; Boric Acid; Edetate Disodium; Guaraprolose (3500 Mpa.S At 1%); Polidronium Chloride; Potassium Chloride; Sodium Chloride; Sorbitol; Water; Hydrochloric Acid; Sodium Hydroxide

Systane Gel Drops
Drug Facts

ACTIVE INGREDIENT

Active Ingredients | Purpose
Polyethylene Glycol 400 0.4% | Lubricant
Propylene Glycol 0.3% | Lubricant

Uses

- for the temporary relief of burning and irritation due to dryness of the eye
- for use as a protectant against further irritation or to relieve dryness of the eye

Warnings

For external use only

Do not use

- if this product changes color or becomes cloudy
- if you are sensitive to any ingredient in this product

When using this product

- do not touch tip of container to any surface to avoid contamination
- replace cap after each use

Stop use and ask a doctor if you experience any of the following:

- eye pain
- changes in vision
- continued redness or irritation of the eye
- condition worsens or persists for more than 72 hours

Keep out of reach of children. If swallowed, get medical help or contact a Poison Control Center right away.

Directions

- shake well before using
- put 1 or 2 drops in the affected eye(s) as needed

Other information

- store at room temperature

Inactive ingredients

aminomethylpropanol, boric acid, edetate disodium, hydroxypropyl guar, POLYQUAD® (polyquaternium-1) 0.001% preservative, potassium chloride, sodium chloride, sorbitol and purified water. May contain hydrochloric acid and/or sodium hydroxide to adjust pH.

Questions?

In the U.S.
call 1-800-757-9195
alcon.medinfo@alcon.com
www.systane.com

PRINCIPAL DISPLAY PANEL

Systane®
LUBRICANT EYE GEL
GEL DROPS
SOOTHING DRY EYE RELIEF
Long-lasting formula
Day or night protection
#1 DOCTOR RECOMMENDED BRAND^1
LIQUID GEL
STERILE
10mL (1/3 FL OZ)
Alcon

SIDE PANEL
TAMPER EVIDENT: For your protection, this bottle has an imprinted seal around the neck. Do not use if seal is damaged or missing at time of purchase.
www.alconpatents.com
Made in USA from domestic and imported materials
Indulge your eyes in this easy-to-use droppable gel. Systane® GEL DROPS forms a protective shield over your eyes to provide enduring relief day or night.
^1 Based on a survey of eye care professionals. Data on file.
300048642-0621
Alcon
Alcon Laboratories, Inc.
Fort Worth, TX 76134 USA

Systane®
LUBRICANT EYE GEL
GEL DROPS
SOOTHING DRY EYE RELIEF
Long-lasting formula
Day or night protection
#1 DOCTOR RECOMMENDED BRANDS1
LIQUID GEL
STERILE
10mL (1/3 fl oz)
Alcon
SIDE PANEL
TAMPER EVIDENT: For your protection, this bottle has an imprinted seal around the neck. Do not use if seal is damaged or missing at time of purchase.
www.alconpatents.com
Country of Origin: Singapore
Indulge your eyes in this easy-to-use droppable gel. Systane® GEL DROPS forms a protective shield over your eyes to provide enduring relief day or night.
ACTUAL SIZE
^1Based on a survey of eye care professionals. Data on file.
Alcon
Alcon Laboratories, Inc.
Fort Worth, TX 76134 USA
300072079-0525